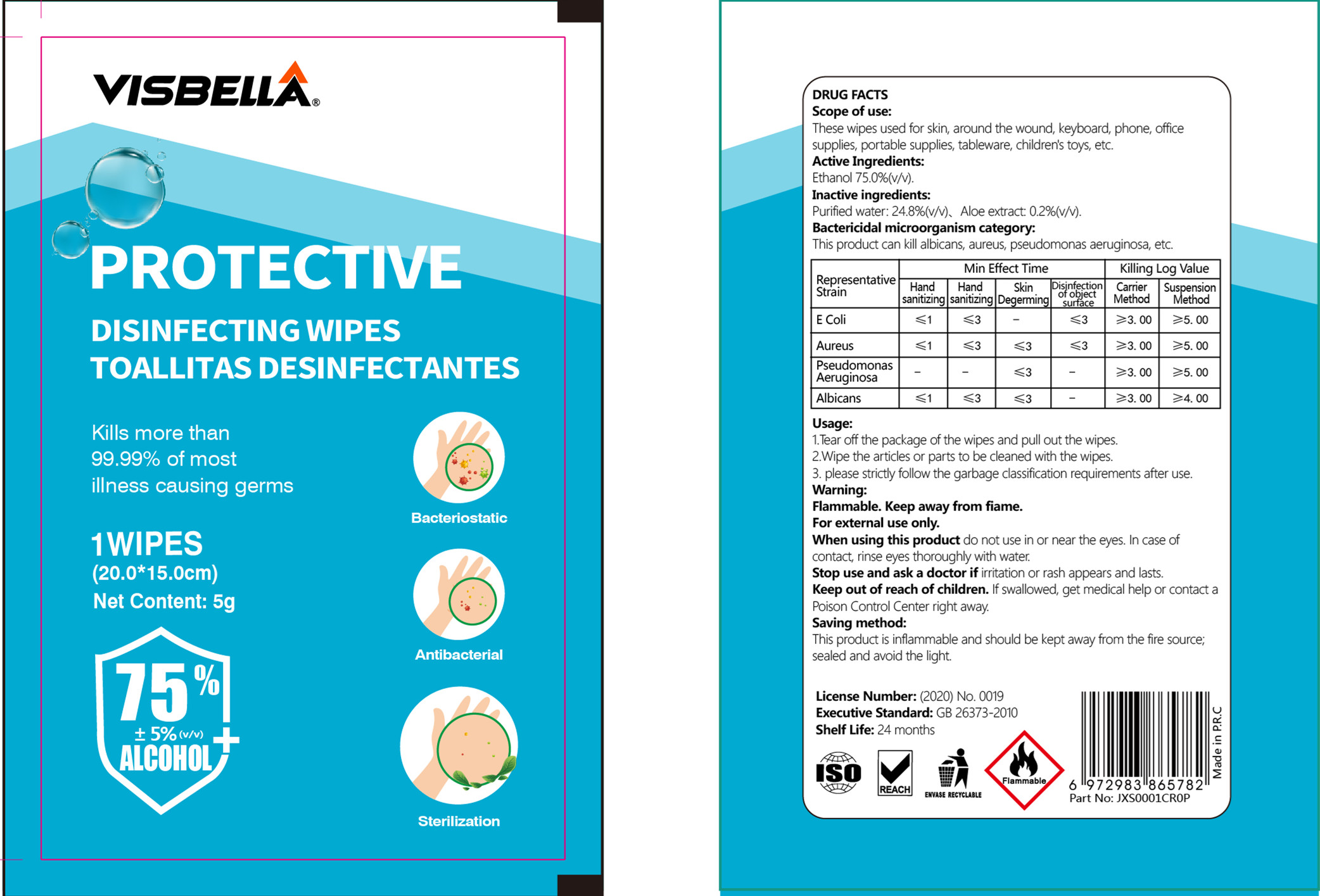 DRUG LABEL: VISBELLA protective disinfecting wipes desinfectar las toallitas
NDC: 40760-005 | Form: CLOTH
Manufacturer: Huzhou Guoneng New Material Co., Ltd.
Category: otc | Type: HUMAN OTC DRUG LABEL
Date: 20200706

ACTIVE INGREDIENTS: ALCOHOL 270 cm2/360 cm2
INACTIVE INGREDIENTS: ALOE; GLYCERIN; CHLORHEXIDINE GLUCONATE

keep out of reach of children

INACTIVE INGREDIENT

aloe extract,chlorhexidine gluconate， glycerin

DOSAGE AND ADMINISTRATION

This product is inflammable and should be kept away from the fire source; sealed and avoid the light.

PURPOSE

Disinfection
Sterilization
No Rinseing

ACTIVE INGREDIENT

alcohol

INDICATIONS AND USAGE

Tear off the package of the wipes and pull out the wipes.

Wipe the articles or parts to be cleaned with the wipes.
please strictly follow the garbage dassfication requirements after use.

WARNINGS

This product is a disinfectant for external use. It is not allowed to be taken orally. If it enters the eyes accidentall, please wash it with clear water.
This product contains alcohol. People who are allergic to alcohol should use it carefully and avoid fire.
Store in a cool place and keep out of reach of the children, avoid high temperature and sunlight.